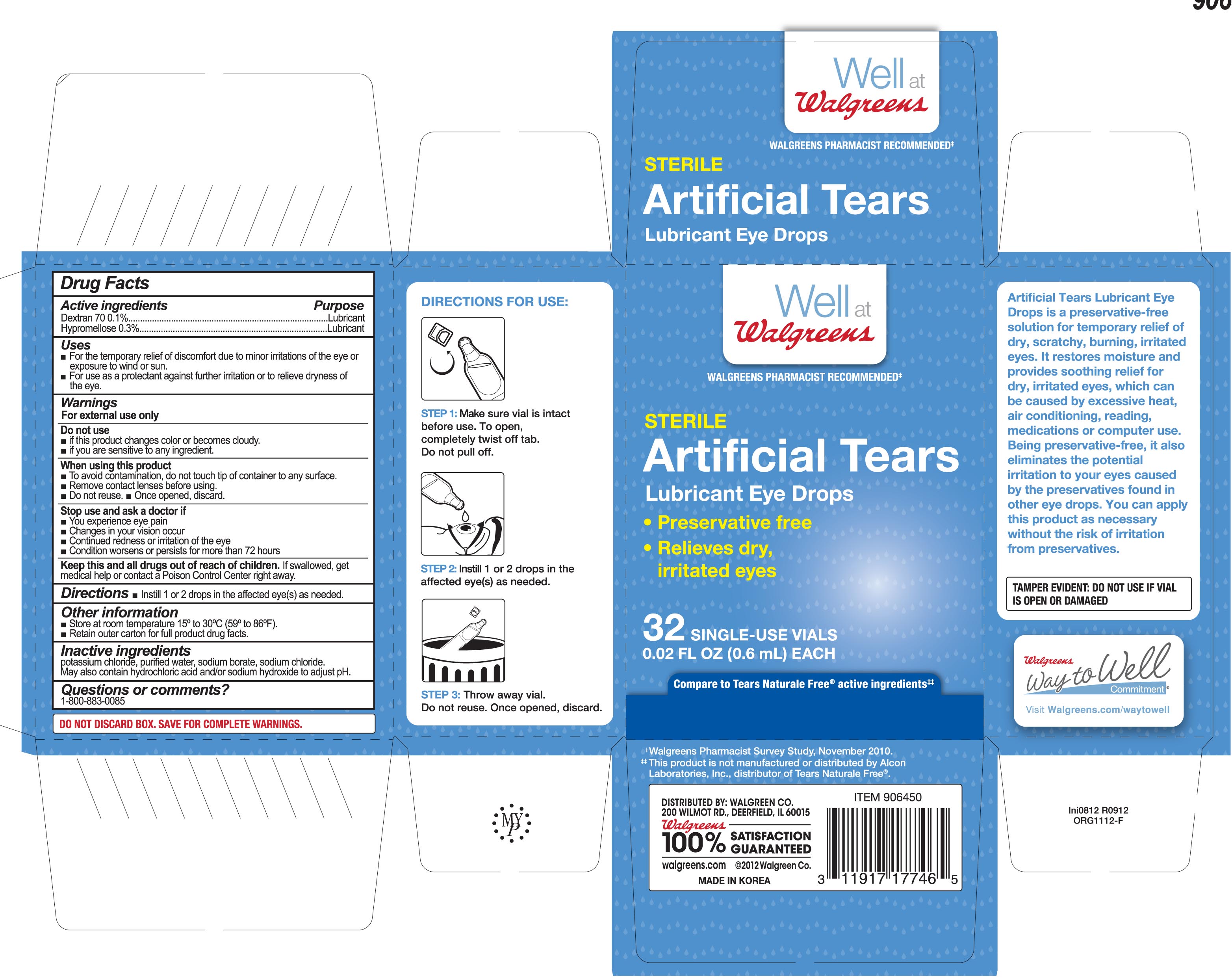 DRUG LABEL: Walgreens Artifical Tears Free
NDC: 0363-7746 | Form: SOLUTION/ DROPS
Manufacturer: Walgreens
Category: otc | Type: HUMAN OTC DRUG LABEL
Date: 20150717

ACTIVE INGREDIENTS: HYPROMELLOSE 2910 (4000 MPA.S) 3 mg/1 mL; DEXTRAN 70 1 mg/1 mL
INACTIVE INGREDIENTS: POTASSIUM CHLORIDE; WATER; SODIUM BORATE; HYDROCHLORIC ACID; SODIUM HYDROXIDE; SODIUM CHLORIDE

Drug Facts

OTC - ACTIVE INGREDIENT SECTION

Dextran 70 0.1%
Hypromellose 0.3%

OTC - PURPOSE SECTION

Lubricant

Lubricant

INDICATIONS & USAGE SECTION

- For the temporary relief of discomfort due to minor irritations of the eye, or to exposure to wind or sun.
- For use as a protectant against further irritation or to relieve dryness of the eye.

WARNINGS SECTION

For external use only

OTC - DO NOT USE SECTION

- If this solution changes color or becomes cloudy.
- If you are sensitive to any ingredient in this product.

OTC - WHEN USING SECTION

- To avoid contamination, do not touch tip of container to any surface.
- Remove contact lenses before using.
- Do not reuse.
- Once opened, discard.

OTC - STOP USE SECTION

- you experience eye pain.
- you experience changes in vision.
- you experience continued redness or irritation of the eye.
- the condition worsens or persists for more than 72 hours.

OTC - KEEP OUT OF REACH OF CHILDREN SECTION

If swallowed, get medical help or contact a Poison Control Center right away.

DOSAGE & ADMINISTRATION SECTION

- Instill one or two drops in the affected eye(s) as needed.

OTHER SAFETY INFORMATION

- Store at room temperature 15° to 30°C (59° to 86°F).
- Retain outer carton for full product drug facts.

INACTIVE INGREDIENT SECTION

Potassium chloride, purified water, sodium borate, sodium chloride. May contain hydrochloric acid and/or sodium hydroxide to adjust pH.

OTC - QUESTIONS SECTION

1-800-883-0085

PRINCIPAL DISPLAY PANEL

Sterile

Artificial Tears

Lubricant Eye Drops

- Preservative free
- Relieves dry, irriated eyes

32 SINGLE-USE VIALS

0.02FL OZ (0.6ML) EACH